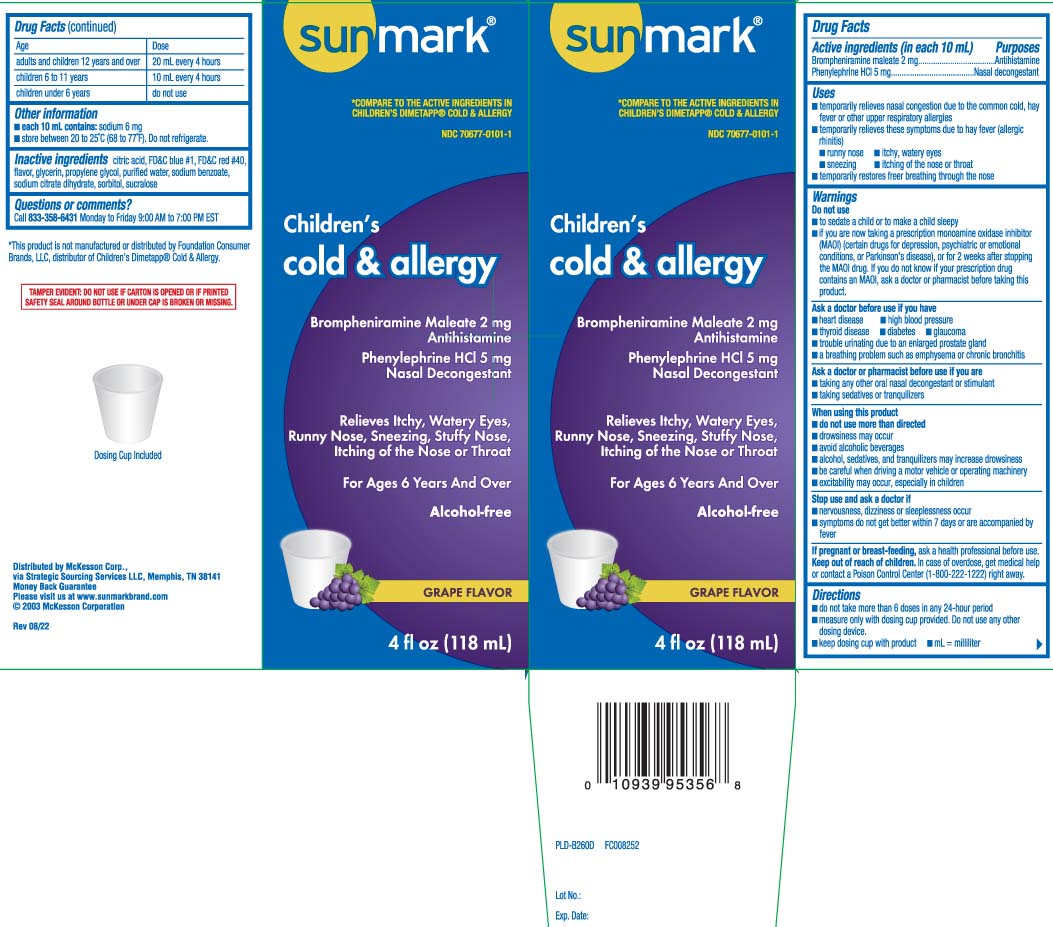 DRUG LABEL: Childrens Cold and Allergy Relief
NDC: 70677-0101 | Form: LIQUID
Manufacturer: Strategic Sourcing Services LLC
Category: otc | Type: HUMAN OTC DRUG LABEL
Date: 20240530

ACTIVE INGREDIENTS: BROMPHENIRAMINE MALEATE 2 mg/10 mL; PHENYLEPHRINE HYDROCHLORIDE 5 mg/10 mL
INACTIVE INGREDIENTS: FD&C BLUE NO. 1; FD&C RED NO. 40; GLYCERIN; PROPYLENE GLYCOL; WATER; SODIUM BENZOATE; TRISODIUM CITRATE DIHYDRATE; SORBITOL; SUCRALOSE; ANHYDROUS CITRIC ACID

Drug Facts

Active ingredients (in each 10 mL)

Brompheniramine maleate 2 mg

Phenylephrine HCI 5 mg

Purposes

Antihistamine

Nasal decongestant

Uses

- temporarily relieves nasal congestion due to the common cold, hay fever or other upper respiratory allergies
- temporarily relieves these symptoms due to hay fever (allergic rhinitis)
  - runny nose
  - itchy, watery eyes
  - sneezing
  - itching of the nose or throat
- temporarily restores freer breathing through the nose

Warnings

Do not use

- to sedate a child or to make a child sleepy
- if you are now taking a prescription monoamine oxidase inhibitor (MAOI) (certain drugs for depression, psychiatric or emotional conditions, or Parkinson's disease), or for 2 weeks after stopping the MAOI drug. If you do not know if your prescription drug contains an MAOI, ask a doctor or pharmacist before taking this product.

Ask a doctor before use if you have

- heart disease
- high blood pressure
- thyroid disease
- diabetes
- glaucoma
- trouble urinating due to an enlarged prostate gland
- a breathing problem such as emphysema or chronic bronchitis

Ask a doctor or pharmacist before use if you are

- taking any other oral nasal decongestant or stimulant
- taking sedatives or tranquilizers

When using this product

- do not use more than directed
- drowsiness may occur
- avoid alcoholic beverages
- alcohol, sedatives, and tranquilizers may increase drowsiness
- be careful when driving a motor vehicle or operating machinery
- excitability may occur, especially in children

Stop use and ask a doctor if

- nervousness, dizziness or sleeplessness occur
- symptoms do not get better within 7 days or are accompanied by fever

If pregnant or breast-feeding,

ask a health professional before use.

Keep out of reach of children.

In case of overdose, get medical help or contact a Poison Control Center (1-800-222-1222) right away.

Directions

- do not take more than 6 doses in any 24-hour period
- measure only with dosing cup provided. Do not use any other dosing device.
- keep dosing cup with product
- mL = milliliter

age | dose
adults and children 12 years and over | 20 mL every 4 hours
children 6 to 11 years | 10 mL every 4 hours
children under 6 years | do not use

Other information

- each 10 mL contains: sodium 6 mg
- store at 20 to 25°C (68 to 77°F). Do not refrigerate.

Inactive ingredients

anhydrous citric acid, FD&C blue #1, FD&C red # 40, flavor, glycerin, propylene glycol, purified water, sodium benzoate, sorbitol, sucralose, trisodium citrate dihydrate

Questions or comments?

Call 1-833-358-6431 Monday to Friday 9:00 AM to 7:00 PM EST

Principal Display Panel

*COMPARE TO THE ACTIVE INGREDIENTS IN CHILDREN'S DIMETAPP® COLD & ALLERGY

Children's

Cold & Allergy

Brompheniramine Maleate 2 mg

Antihistamine

Phenylephrine HCl 5 mg

Nasal Decongestant

Relieves Itchy, Watery Eyes, Runny Nose, Sneezing, Stuffy Nose, Itchy of the Nose or Throat

For Ages 6 Years And Over

Alcohol-free

GRAPE FLAVOR

FL OZ (mL)

*This product is not manufactured or distributed by Foundation Consumer Brands, LLC, distributors of Children's Dimetapp® Cold & Allergy.

TAMPER EVIDENT: DO NOT USE IF CARTON IS OPENED OR IF PRINTED SAFETY SEAL AROUND BOTTLE OR UNDER CAP IS BROKEN OR MISSING.

Distributed by McKesson Corp.,

via Strategic Sourcing Services LLC, Memphis, TN 38141

www.sunmarkbrand.com

Package Label

SUNMARK Children's Cold & Allergy Grape Flavor